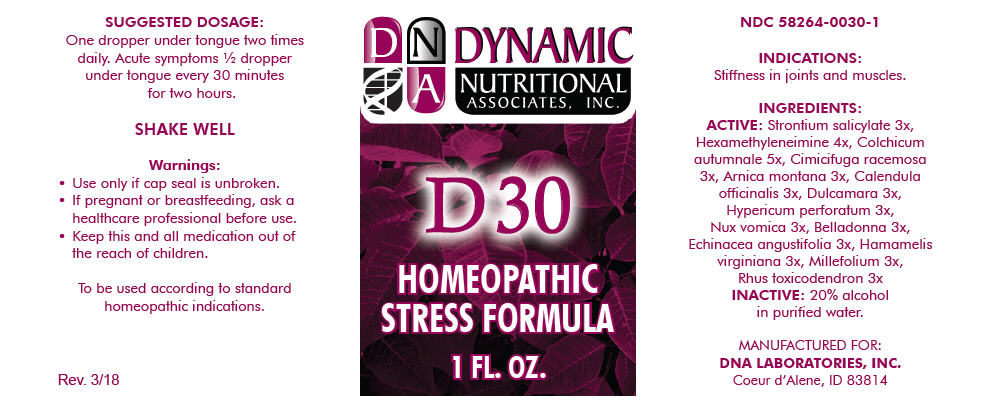 DRUG LABEL: D-30
NDC: 58264-0030 | Form: SOLUTION
Manufacturer: DNA Labs, Inc.
Category: homeopathic | Type: HUMAN OTC DRUG LABEL
Date: 20250113

ACTIVE INGREDIENTS: STRONTIUM SALICYLATE 3 [hp_X]/1 mL; METHENAMINE 4 [hp_X]/1 mL; COLCHICUM AUTUMNALE BULB 5 [hp_X]/1 mL; BLACK COHOSH 3 [hp_X]/1 mL; ARNICA MONTANA 3 [hp_X]/1 mL; CALENDULA OFFICINALIS FLOWERING TOP 3 [hp_X]/1 mL; SOLANUM DULCAMARA WHOLE 3 [hp_X]/1 mL; HYPERICUM PERFORATUM 3 [hp_X]/1 mL; STRYCHNOS NUX-VOMICA SEED 3 [hp_X]/1 mL; ATROPA BELLADONNA 3 [hp_X]/1 mL; ECHINACEA ANGUSTIFOLIA 3 [hp_X]/1 mL; HAMAMELIS VIRGINIANA ROOT BARK/STEM BARK 3 [hp_X]/1 mL; ACHILLEA MILLEFOLIUM 3 [hp_X]/1 mL; TOXICODENDRON PUBESCENS LEAF 3 [hp_X]/1 mL
INACTIVE INGREDIENTS: ALCOHOL; WATER

D-30

NDC 58264-0030-1

INDICATIONS

PURPOSE

Stiffness in joints and muscles.

INGREDIENTS

ACTIVE

Strontium salicylate 3x, Hexamethyleneimine 4x, Colchicum autumnale 5x, Cimicifuga racemosa 3x, Arnica montana 3x, Calendula officinalis 3x, Dulcamara 3x, Hypericum perforatum 3x, Nux vomica 3x, Belladonna 3x, Echinacea angustifolia 3x, Hamamelis virginiana 3x, Millefolium 3x, Rhus toxicodendron 3x

INACTIVE

20% alcohol in purified water.

SUGGESTED DOSAGE

One dropper under tongue two times daily. Acute symptoms ½ dropper under tongue every 30 minutes for two hours.

STORAGE AND HANDLING

SHAKE WELL

Warnings

- Use only if cap seal is unbroken.

PREGNANCY OR BREAST FEEDING

- If pregnant or breastfeeding, ask a healthcare professional before use.

KEEP OUT OF REACH OF CHILDREN

- Keep this and all medication out of the reach of children.

To be used according to standard homeopathic indications.

PRINCIPAL DISPLAY PANEL - 1 FL. OZ. Bottle Label

DYNAMIC
NUTRITIONAL
ASSOCIATES, INC.

D 30

HOMEOPATHIC
STRESS FORMULA

1 FL. OZ.